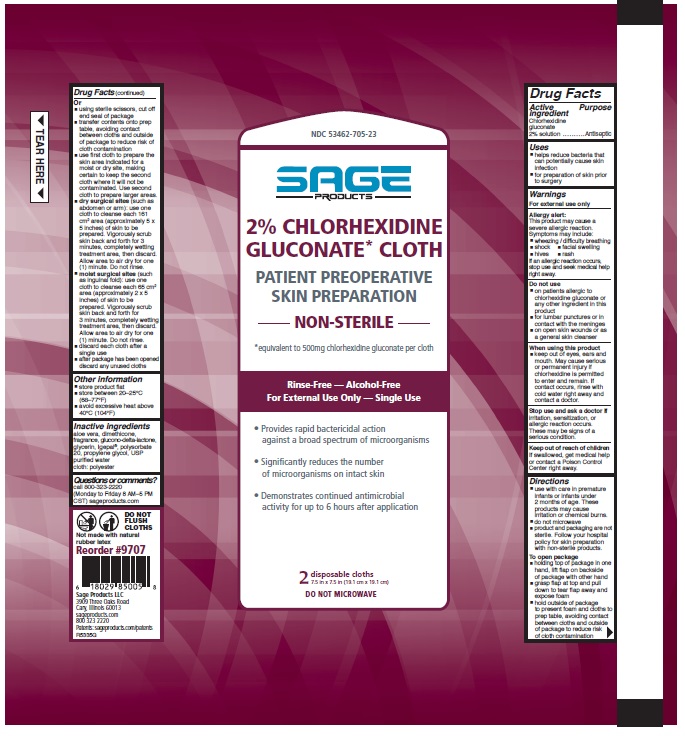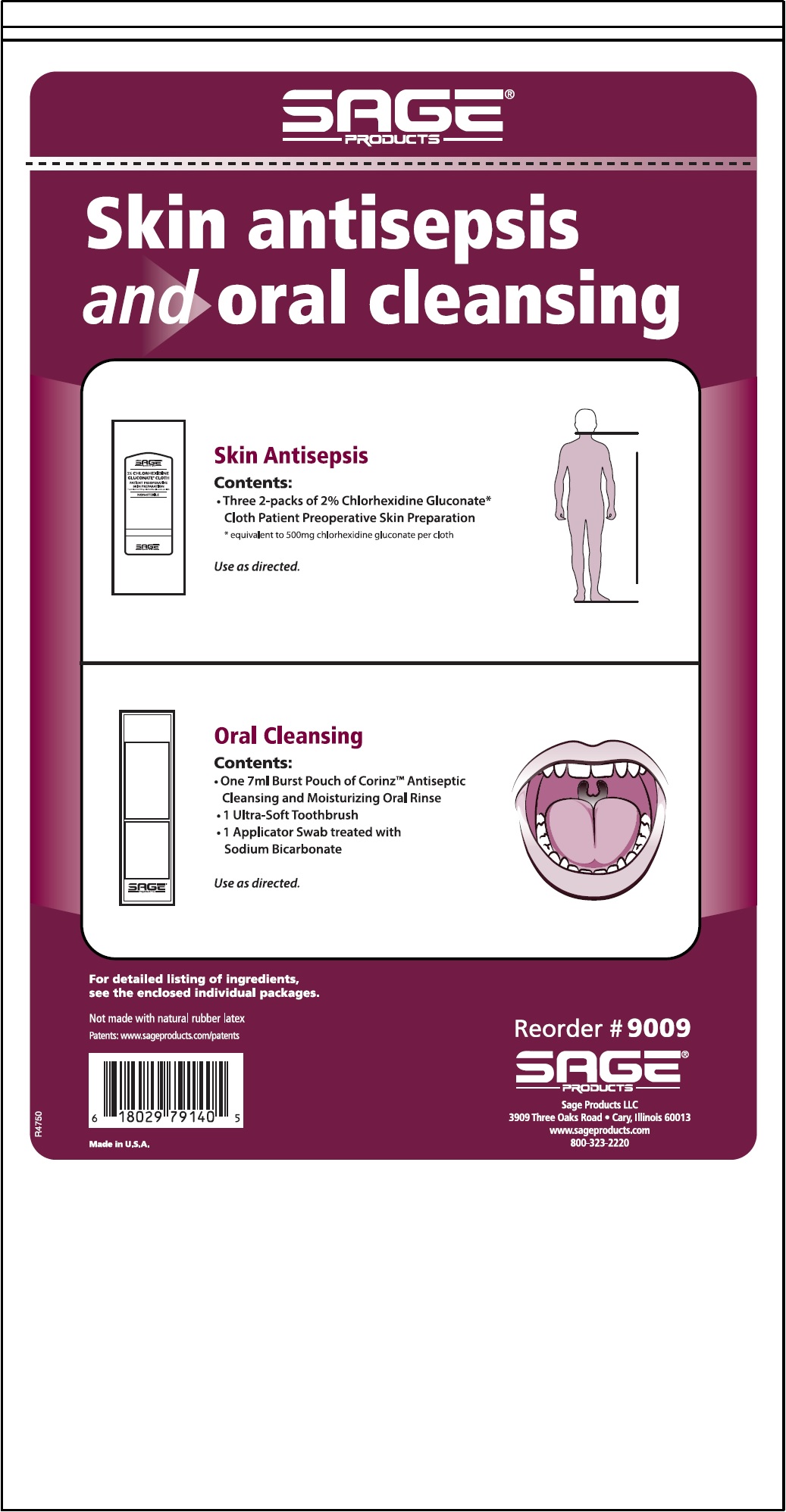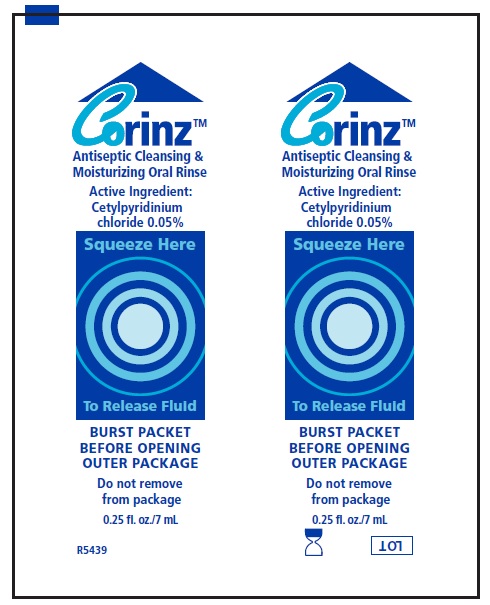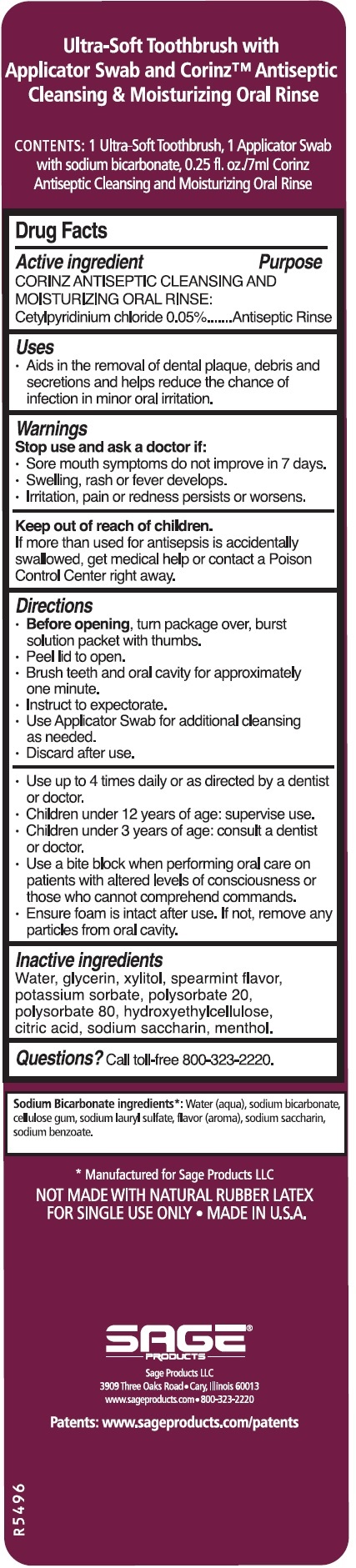 DRUG LABEL: Skin Antisepsis, Oral Cleansing and Nasal Antisepsis System
NDC: 53462-009 | Form: KIT | Route: TOPICAL
Manufacturer: Sage Products, LLC
Category: otc | Type: HUMAN OTC DRUG LABEL
Date: 20190724

ACTIVE INGREDIENTS: CHLORHEXIDINE GLUCONATE 500 mg/1 1; CETYLPYRIDINIUM CHLORIDE 0.5 mg/1 mL
INACTIVE INGREDIENTS: WATER; NONOXYNOL-9; POLYSORBATE 20; DIMETHICONE 350; PROPYLENE GLYCOL; ALOE VERA LEAF; GLYCERIN; GLUCONOLACTONE; WATER; GLYCERIN; XYLITOL; POTASSIUM SORBATE; POLYSORBATE 20; POLYSORBATE 80; HYDROXYETHYL CELLULOSE (4000 MPA.S AT 1%); CITRIC ACID MONOHYDRATE; SACCHARIN SODIUM; MENTHOL, UNSPECIFIED FORM

Nose to Toes: Skin Antisepsis, Oral Cleansing and Nasal Antisepsis System

Drug Facts

Active Ingredient | Purpose
Corinz Antiseptic Cleansing and Moisturizing Oral Rinse:
Cetylpyridinium Chloride 0.05% | Antiseptic Rinse

Use

Helps reduce chance of infection in minor oral irritation.

Warnings

Stop use and ask a doctor if:

- Sore mouth symptoms do not improve in 7 days.
- Swelling, rash or fever develops.
- Irritation, pain or redness persists or worsens.

Keep out of reach of children.

If more than used for antisepsis is accidentally swallowed, get medical help or contact a Poison Control Center right away.

Directions

- Before opening, turn package over, burst solution packet with thumbs.
- Peel lid to open.
- Brush teeth and oral cavity for approximately one minute.
- Instruct to expectorate.
- Use Applicator Swab for additional cleansing as needed.
- Discard after use.
- Use up to 4 times daily or as directed by a dentist or doctor.
- Children under 12 yeras of age: supervise use.
- Children under 3 years of age: consult a dentist or doctor.
- Use a bite block when performing oral care on patients with altered levels of consciousness or those who cannot comprehend commands.
- Ensure foam is intact after use. If not, remove any particles from oral cavity.

Inactive Ingredients

Water, glycerin, xylitol, spearmint flavor, potassium sorbate, polysorbate 20, polysorbate 80, hydroxyethylcellulose, citric acid, sodium saccharin, menthol.

Drugs Facts

CHG 2%
Active Ingredient | Purpose
Chlorhexidine gluconate 2% solution | Antiseptic

Uses

- helps reduce bacteria that can potentially cause skin infection
- for preparation of skin prior to surgery

Warnings

For external use only

Allergy alert:

This product may cause a severe allergic reaction. Symptoms may include:

- wheezing/difficulty breathing
- shock
- facial swelling
- hives
- rash

If an allergic reaction occurs, stop use and seek medical help right away.

Do not use

- on patients allergic to chlorhexidine gluconate or any other ingredient in this product
- for lumbar punctures or in contact with the meninges
- on open skin wounds or as a general skin cleanser

When using this product

- keep out of eyes, ears and mouth. May cause serious or permanent injury if chlorhexidine is permitted to enter and remain. If contact occurs, rinse with cold water right away and contact a doctor.

Stop use and ask a doctor if irritation, sensitization or allergic reaction occurs. These may be signs of a serious condition.

Keep out of reach of children

If swallowed, get medical help or contact a Poison Control Center right away.

Directions

- use with care in premature infants or infants under 2 months of age. These products may cause irritation or chemical burns.
- do not microwave
- product and packaging are not sterile. Follow your hospital policy for skin preparation with non-sterile products.

To open package

- holding top of package in one hand, lift flap on backside of package with other hand
- grasp flap at top and pull down to tear flap away and expose foam
- hold outside of package to present foam and cloths to prep table, avoiding contact between cloths and outside of package to reduce risk of cloth contamination.

Or

- using sterile scissors, cut off end seal of package
- transfer contents onto prep table, avoiding contact between cloths and outside of package to reduce risk of cloth contamination
- use first cloth to prepare the skin area indicated for a moist or dry site, making certain to keep the second cloth where it will not be contaminated. Use second cloth to prepare larger areas.
- dry surgical sites (such as abdomen or arm): use one cloth to cleanse each 161 cm² area (approximately 5 x 5 inches) of skin to be prepared. Vigorously scrub skin back and forth for 3 minutes, completely wetting treatment area, then discard. Allow area to air dry for one (1) minute. Do not rinse.
- moist surgical sites (such as inguinal fold): use one cloth to cleanse each 65 cm² area (approximately 2 x 5 inches) of skin to be prepared. Vigorously scrub skin back and forth for 3 minutes, completely wetting treatment area, then discard. Allow area to air dry for one (1) minute. Do not rinse.
- discard each cloth after a single use
- after package has been opened discard any unused cloths

Other information

- store product flat
- store between 20-25°C (68-77°F)
- avoid excessive heat above 40°C (104°F)

Inactive Ingredients

aloe vera, dimethicone, fragrance, glucono-delta-lactone, glycerin, Igepal®, polysorbate 20, propylene glycol, USP purified water

cloth: polyester

Questions or comments?

call toll-free 800-323-2220

(Monday to Friday 8 AM - 5 PM CST)

www.sageproducts.com

DO NOT FLUSH CLOTHS. Not made with Natural Rubber Latex.

Patents:

www.sageproducts.com/patents